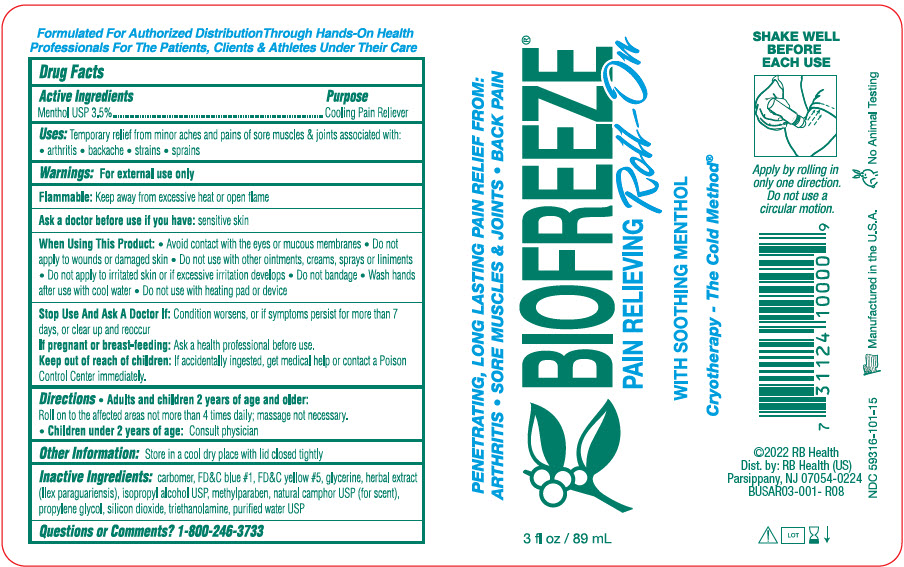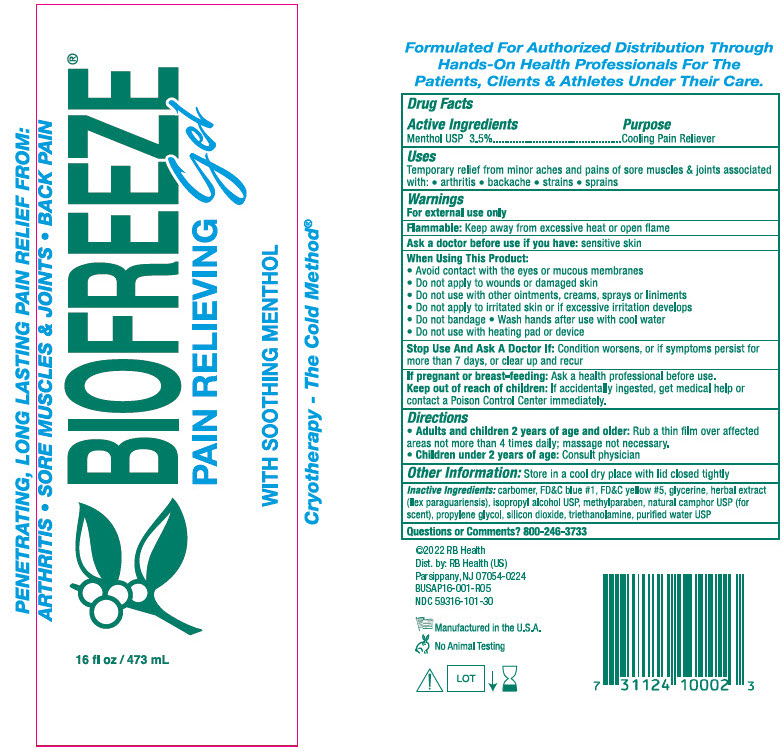 DRUG LABEL: Biofreeze
NDC: 59316-101 | Form: GEL
Manufacturer: RB Health (US) LLC
Category: otc | Type: HUMAN OTC DRUG LABEL
Date: 20241227

ACTIVE INGREDIENTS: MENTHOL, UNSPECIFIED FORM 35 mg/1 mL
INACTIVE INGREDIENTS: FD&C BLUE NO. 1; FD&C YELLOW NO. 5; GLYCERIN; ISOPROPYL ALCOHOL; METHYLPARABEN; CAMPHOR (NATURAL); PROPYLENE GLYCOL; SILICON DIOXIDE; TROLAMINE; WATER

Biofreeze Pain Relieving Gel

Active Ingredients

Menthol USP 3.5%

Purpose

Cooling Pain Reliever

Uses

Temporary relief from minor aches and pains of sore muscles and joints associated with: arthritis - backache - strains - sprain

Warnings

For external use only.

Flammable

Keep away from excessive heat or open flame

Ask a doctor before use if you have:

sensitive skin

When Using This Product

- Avoid contact with the eyes or mucous membranes
- Do not apply to wounds or damaged skin
- Do not use with other ointments, creams, sprays or liniments
- Do not apply to irritated skin or if excessive irritation develops
- Do not bandage
- Wash hands after use with cool water
- Do not use with heating pad or device

Stop Use And Ask A Doctor If:

Condition worsens, or if symptoms persist for more than 7 days, or clear up and recur.

If pregnant or breastfeeding:

Ask a health professional before use.

Keep out of the reach of children:

If accidentally ingested, get medical help or contact a Poison Control Center immediately.

Directions

- Adults and children 2 years of age and older: Rub a thin film over affected areas not more than 4 times daily; massage not necessary.
- Children under 2 years of age : Consult physician

Other Information:

Store in a cool dry place with lid closed tightly

Inactive ingredients

- carbomer, FD and C blue # 1, FD and C yellow # 5, glycerine, herbal extract (llex paraguariensis), isopropyl alcohol USP, methylparaben, natural camphor USP (for scent), propylene glycol, silicon dioxide, triethanolamine, purified water USP

Questions or Comments?

800-246-3733

PRINCIPAL DISPLAY PANEL - 89 mL Bottle Applicator Label

PENETRATING, LONG LASTING PAIN RELIEF FROM:
ARTHITIS • SORE MUSCLES & JOINTS • BACK PAIN

BIOFREEZE®
PAIN RELIEVING Roll-On

WITH SOOTHING MENTHOL

Cryotherapy - The Cold Method®

3 fl oz / 89 mL

PRINCIPAL DISPLAY PANEL - 473 mL Bottle Pump Label

PENETRATING, LONG LASTING PAIN RELIEF FROM:
ARTHITIS • SORE MUSCLES & JOINTS • BACK PAIN

BIOFREEZE®
PAIN RELIEVING gel

WITH SOOTHING MENTHOL

Cryotherapy - The Cold Method®

16 fl oz / 473 mL